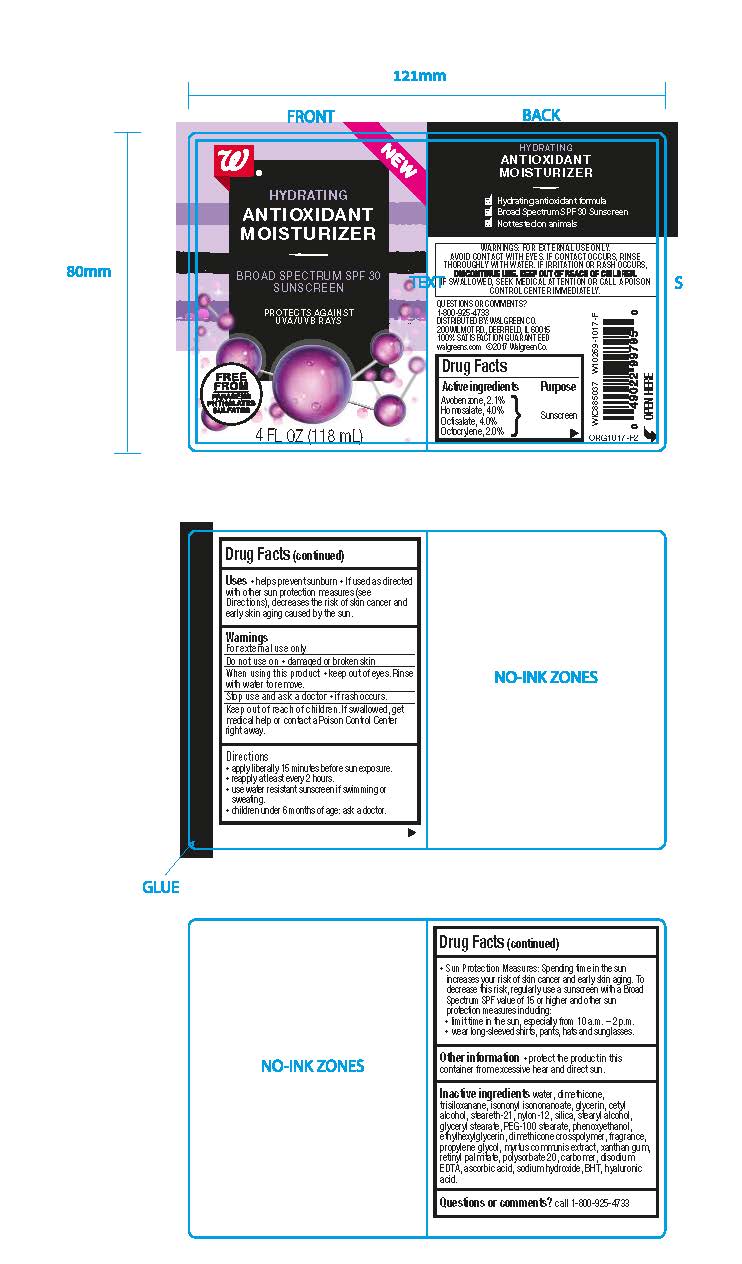 DRUG LABEL: Hydrating Antioxidant Moiturizer
NDC: 0363-0540 | Form: CREAM
Manufacturer: Walgreen Company
Category: otc | Type: HUMAN OTC DRUG LABEL
Date: 20171109

ACTIVE INGREDIENTS: AVOBENZONE 2.478 g/118 mL; HOMOSALATE 4.72 g/118 mL; OCTISALATE 4.72 g/118 mL; OCTOCRYLENE 2.36 1/118 mL
INACTIVE INGREDIENTS: WATER; DIMETHICONE; TRISILOXANE; ISONONYL ISONONANOATE; GLYCERIN; CETYL ALCOHOL; STEARETH-21; NYLON-12; SILICON DIOXIDE; STEARYL ALCOHOL; GLYCERYL MONOSTEARATE; PEG-100 STEARATE; PHENOXYETHANOL; ETHYLHEXYLGLYCERIN; DIMETHICONE CROSSPOLYMER (450000 MPA.S AT 12% IN CYCLOPENTASILOXANE); PROPYLENE GLYCOL; MYRTUS COMMUNIS LEAF; XANTHAN GUM; VITAMIN A PALMITATE; POLYSORBATE 20; CARBOXYPOLYMETHYLENE; EDETATE DISODIUM ANHYDROUS; ASCORBIC ACID; SODIUM HYDROXIDE; BUTYLATED HYDROXYTOLUENE; HYALURONIC ACID

Active ingredients

Avobenzone, 2.1%

Homosalate, 4.0%

Octisalate, 4.0%

Octocrylene, 2.0%

Purpose

Sunscreen

INDICATIONS AND USAGE

Uses •helps prevent sunburn •If used as directed

with other protection measures (see

Directions), decreases the risk of skin cancer and

early skin aging caused by the sun.

Warnings

For external use only.

Do not use on •damaged or broken skin

When using this product •keep out of eyes. Rinse

with water to remove.

Stop use and ask a doctor •if rash occurs.

WARNINGS: FOR EXTERNAL USE ONLY.

AVOID CONTACT WITH EYES. IF CONTACT OCCURS, RINSE

THOROUGHLY WITH WATER. IF IRRITATION OR RASH OCCURS,

DISCONTINUE USE. KEEP OUT OF REACH OF CHILDREN.

IF SWALLOWED, SEEK MEDICAL ATTENTION OR CONTACT POISON

CONTROL CENTER RIGHT AWAY.

QUESTIONS OR COMMENTS?

call 1-800-925-4733

Keep out of reach of children. If swallowed, get

medical help or contact a Poison Control Center

right away.

Directions

•apply liberally 5 minutes before sun exposure

•reapply at least every 2 hours

•use water resistant sunscreen if swimming or

sweating.

•children under 6 months of age: ask a doctor.

•Sun Protection Measures: spending time in the sun

increases your risk of skin cancer and early skin aging. To

decrease this risk, regularly use a sunscreen with a Broad

Spectrum SPF value of 15 or higher and other sun

protection measures including:

•limit time in the sun, specially from 10 a.m. - 2 p.m.

•wear long-sleeved shirts, pants, hats and sunglasses.

Other information •protect the product in this

container from excessive heat and direct sun.

Inactive ingredients Water, Dimethicone,

Trisiloxanane, Isononyl Isononanoate, Glycerin, Cetyl Alcohol,

Steareth-21, Nylon-12, Silica, Stearyl Alcohol, Glyceryl Stearate,

PEG-100 Stearate, Phenoxyethanol, Ethylhexylglycerin,

Dimethicone Crosspolymer, Fragrance, Propylene Glycol,

Myrtus Communis Extract, Xanthan Gum, Retinyl Palmitate, Polysorbate 20, Carbomer,

Disodium EDTA, Ascorbic Acid, Sodium Hydroxide, ,BHT, Hyaluronic Acid.